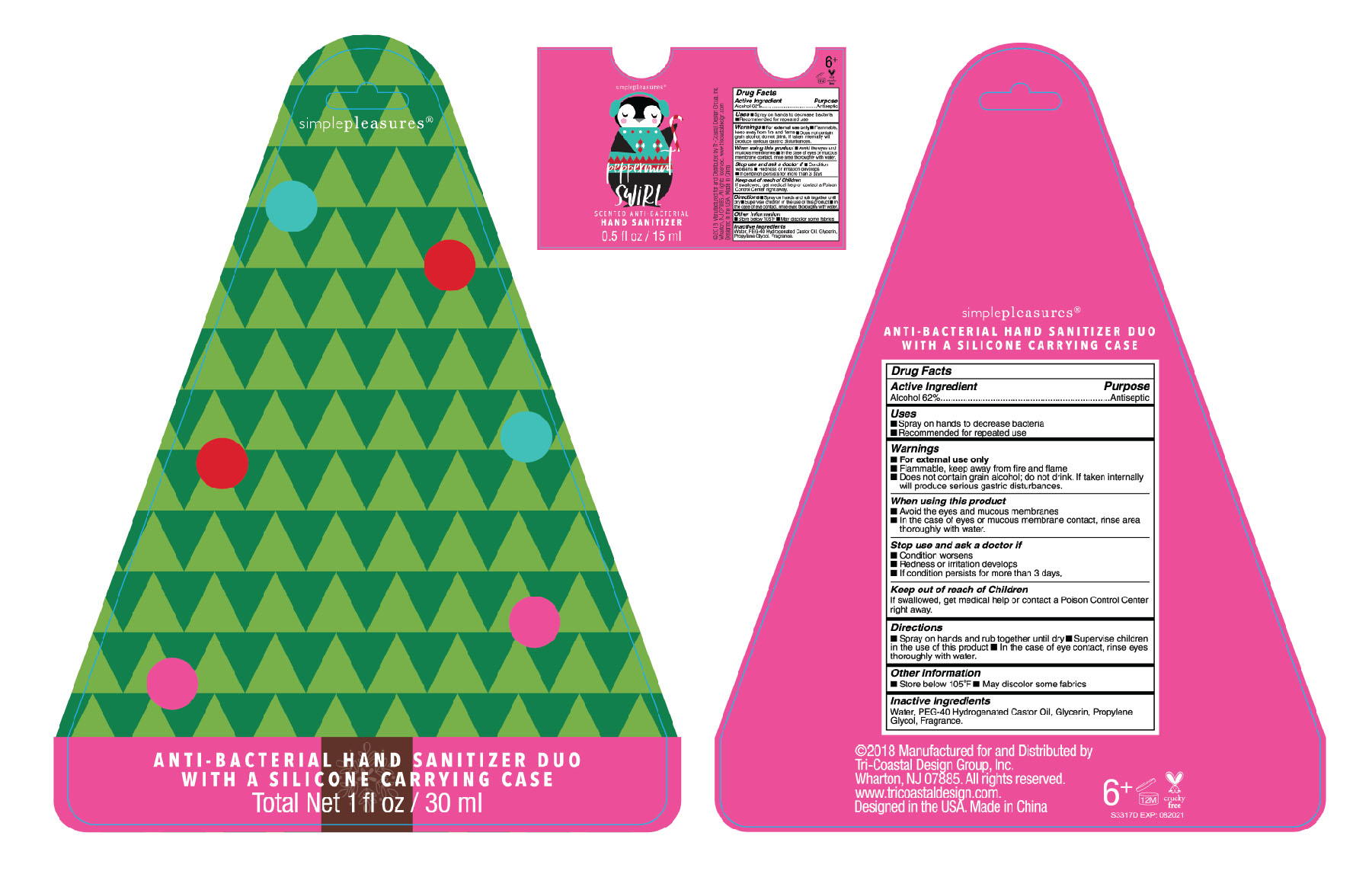 DRUG LABEL: simplepleasures
NDC: 49852-168 | Form: LIQUID
Manufacturer: Tri-Coastal Design Company Inc.
Category: otc | Type: HUMAN OTC DRUG LABEL
Date: 20180726

ACTIVE INGREDIENTS: ALCOHOL 62 g/100 mL
INACTIVE INGREDIENTS: WATER; GLYCERIN; POLYOXYL 40 HYDROGENATED CASTOR OIL; PROPYLENE GLYCOL

Drug Facts

Active Ingredient

Alcohol 62%

Purpose

Antiseptic

Uses

■ Spray on hands to decrease bacteria

■ Recommended for repeated use

Warnings

■ For external use only ■ Flammable, keep away from fire and flame ■ Does not contain grain alcohol; do not drink, if taken internally will produce serious gastric disturbances

When using this product

■ Avoid the eyes and mucous membranes ■ In the case of eyes or mucous membrane contact; rinse area thoroughly with water

Stop use and ask a doctor if

■ Condition worsens ■ Redness or irritation develops ■ If condition persists for more than 3 days

Keep out of reach of children

If swallowed, get medical help or Poison Control Center right away.

Directions

■ Spray on hands and rub together until dry ■ Supervise children in the use of this product ■ In the case of eye contact, rinse eyes thoroughly with water.

Other information

■ Store below 105ºF ■ May discolor some fabrics

Inactive Ingredients

Water, PEG-40 Hydrogenated Castor Oil, Glycerin, Propylene Glycol, Fragrance